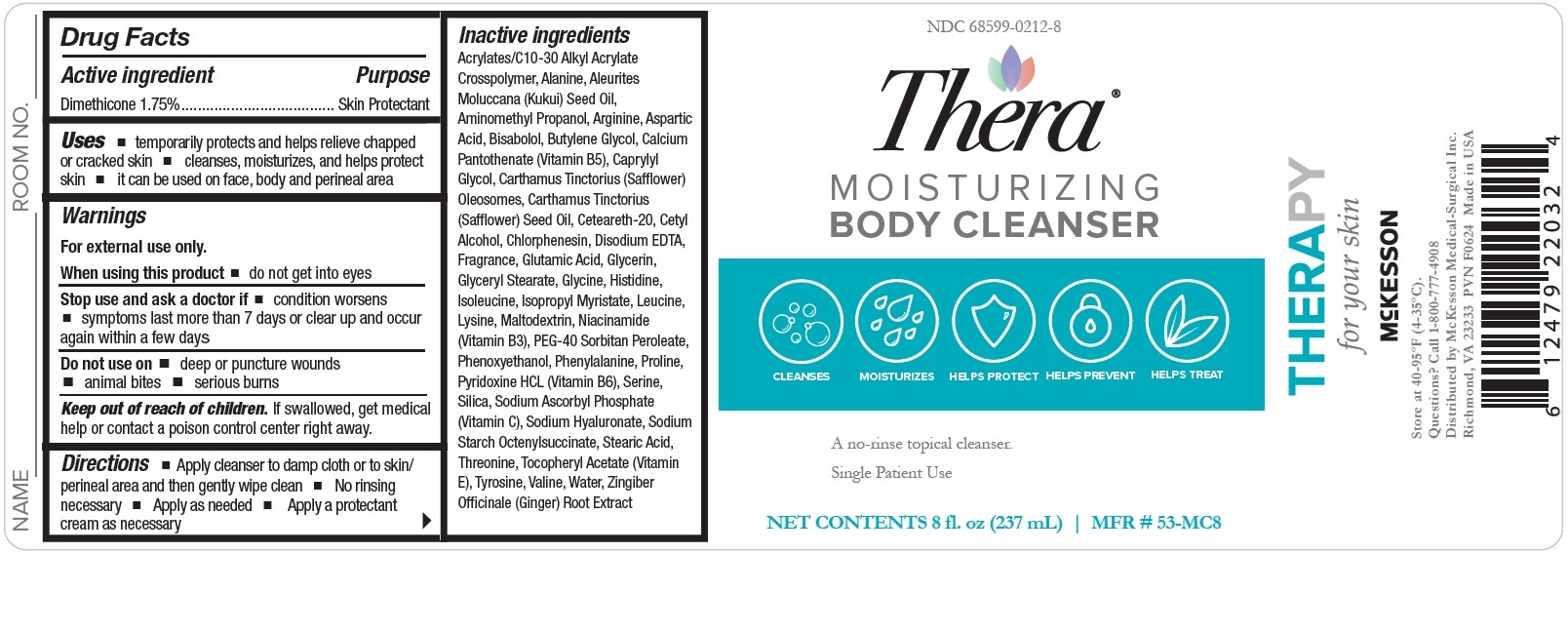 DRUG LABEL: Dimethicone
NDC: 68599-0212 | Form: LIQUID
Manufacturer: McKesson
Category: otc | Type: HUMAN OTC DRUG LABEL
Date: 20240614

ACTIVE INGREDIENTS: DIMETHICONE 17.5 ug/1 mg
INACTIVE INGREDIENTS: OCTENYLSUCCINIC ACID; LEUCINE; SILICON DIOXIDE; PEG-9 DIGLYCIDYL ETHER/SODIUM HYALURONATE CROSSPOLYMER; POLYOXYL 20 CETOSTEARYL ETHER; GLYCERYL STEARATE SE; PEG-40 SORBITAN PEROLEATE; PYRIDOXINE HYDROCHLORIDE; WATER; SAFFLOWER OIL; STEARIC ACID; CETYL ALCOHOL; ASPARTIC ACID; PROLINE; GLYCINE; TYROSINE; PHENYLALANINE; ALANINE; SODIUM ASCORBYL PHOSPHATE; SERINE; VALINE; THREONINE; LYSINE; HISTIDINE; ARGININE; GLUTAMIC ACID; .ALPHA.-TOCOPHEROL ACETATE; NIACINAMIDE; GINGER; KUKUI NUT OIL; GLYCERIN; BUTYLENE GLYCOL; CAPRYLYL GLYCOL; CHLORPHENESIN; ISOPROPYL MYRISTATE; MALTODEXTRIN; ISOLEUCINE; PHENOXYETHANOL; CARTHAMUS TINCTORIUS (SAFFLOWER) OLEOSOMES; CALCIUM PANTOTHENATE; CARBOMER INTERPOLYMER TYPE A (55000 CPS); AMINOMETHYLPROPANOL; .BETA.-BISABOLOL; MAGNESIUM DISODIUM EDTA

Moisturizing Body Cleanser

Drug Facts

Active ingredient
Dimethicone 1.75%

Purpose
Skin Protectant

Uses

- temporarily protects and helps relieve chapped or cracked skin
- cleanses, moisturizes, and helps protect skin
- it can be used on face, body and perineal area

Warnings
For external use only.
When using this product

- do not get into eyes

Do not use on

- deep or puncture wounds
- animal bites
- serious burns

Stop use and ask a doctor if

- condition worsens
- symptoms last more than 7 days or clear up and occur again within a few days

Keep out of reach of children.
If swallowed, get medical help or contact a poison control center right away.

Directions

- Apply cleanser to damp cloth or to skin/ perineal area and then gently wipe clean
- No rinsing necessary
- Apply as needed
- Apply a protectant cream as necessary

OTHER SAFETY INFORMATION

Store at 40-95ºF (4-35ºC)

Inactive Ingredients: Acrylates/C10-30 Alkyl Acrylate
Crosspolymer, Alanine, Aleurites
Moluccana (Kukui) Seed Oil,
Aminomethyl Propanol, Arginine, Aspartic
Acid, Bisabolol, Butylene Glycol, Calcium
Pantothenate (Vitamin B5), Caprylyl
Glycol, Carthamus Tinctorius (Safflower)
Oleosomes, Carthamus Tinctorius
(Safflower) Seed Oil, Ceteareth-20, Cetyl
Alcohol, Chlorphenesin, Disodium EDTA,
Fragrance, Glutamic Acid, Glycerin,
Glyceryl Stearate, Glycine, Histidine,
Isoleucine, Isopropyl Myristate, Leucine,
Lysine, Maltodextrin, Niacinamide
(Vitamin B3), PEG-40 Sorbitan Peroleate,
Phenoxyethanol, Phenylalanine, Proline,
Pyridoxine HCL (Vitamin B6), Serine,
Silica, Sodium Ascorbyl Phosphate
(Vitamin C), Sodium Hyaluronate, Sodium
Starch Octenylsuccinate, Stearic Acid,
Threonine, Tocopheryl Acetate (Vitamin
E), Tyrosine, Valine, Water, Zingiber
Officinale (Ginger) Root Extract

Questions?
Call 1-800-777-4908

PACKAGE LABEL

NDC 68599-0212-8
Thera
MOISTURIZING BODY CLEANSER
A no-rinse topical cleanser
Single Patient Use
NET CONTENTS 8 fl. oz (237 mL)
MFR # 53-MC8